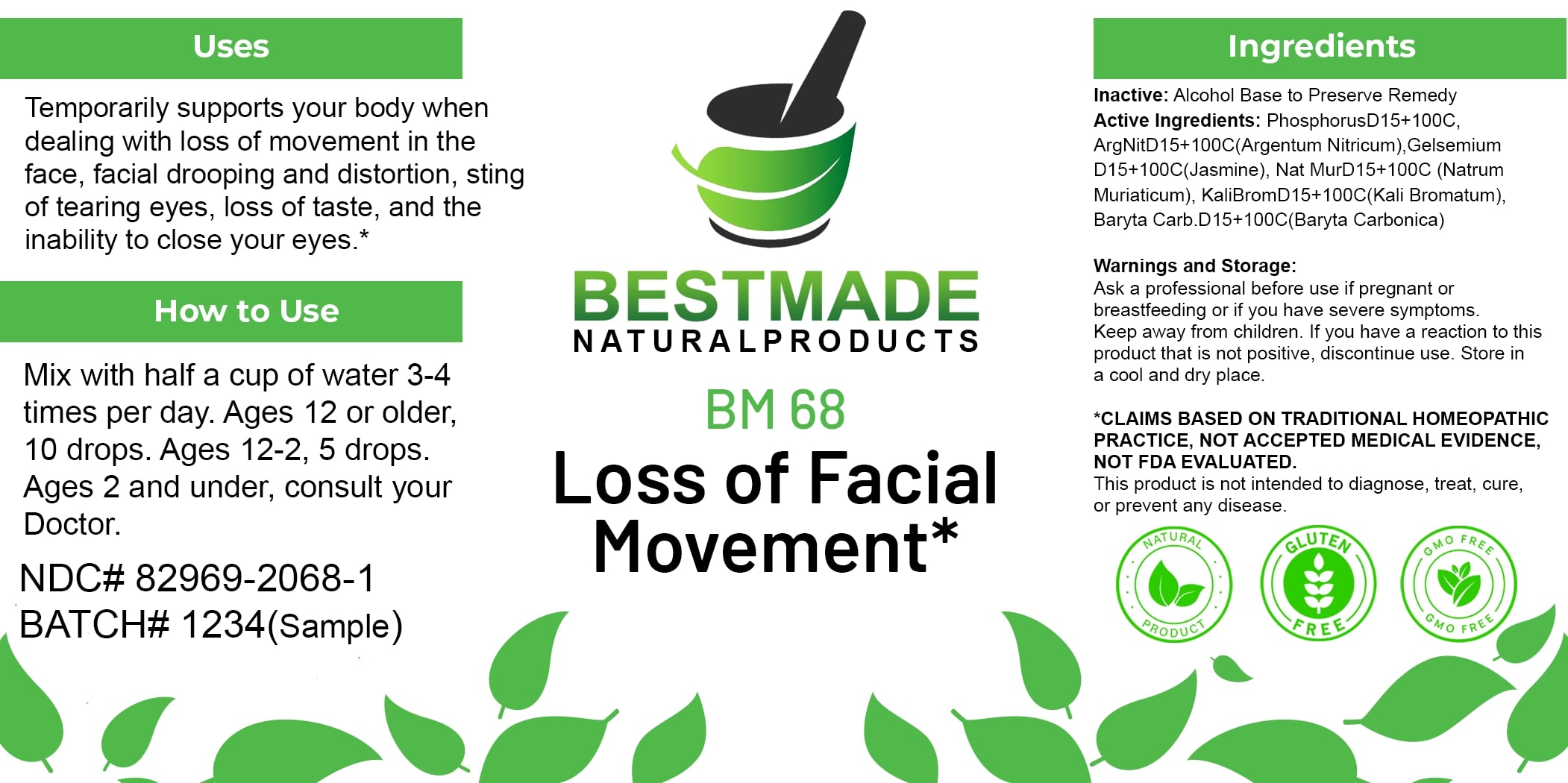 DRUG LABEL: Bestmade Natural Products BM68
NDC: 82969-2068 | Form: LIQUID
Manufacturer: Bestmade Natural Products
Category: homeopathic | Type: HUMAN OTC DRUG LABEL
Date: 20250130

ACTIVE INGREDIENTS: SILVER NITRATE 30 [hp_C]/30 [hp_C]; SODIUM CHLORIDE 30 [hp_C]/30 [hp_C]; GELSEMIUM SEMPERVIRENS ROOT 30 [hp_C]/30 [hp_C]; POTASSIUM BROMIDE 30 [hp_C]/30 [hp_C]; PHOSPHORUS 30 [hp_C]/30 [hp_C]; BARIUM CARBONATE 30 [hp_C]/30 [hp_C]
INACTIVE INGREDIENTS: ALCOHOL 30 [hp_C]/30 [hp_C]

BM68

DOSAGE AND ADMINISTRATION

How to Use

Mix with half a cup of water 3-4 times per day. Ages 12 or older, 10 drops. Ages 12-2, 5 drops. Ages 2 and under, consult your Doctor.

INACTIVE INGREDIENT

Ingredients

Inactive: Alcohol Base to Preserve Remedy

ACTIVE INGREDIENT

Active Ingredients: Phosphorus D15+100C, Arg Nit D15+100C (Argentum Nitricum), Gelsemium D15+100C (Jasmine), Nat Mur D15+100C (Natrum Muriaticum), Kali Brom D15+100C (Kali Bromatum), Baryta Carb. D15+100C (Baryta Carbonica)

Uses

Temporarily supports your body when dealing with loss of movement in the face, facial drooping and distortion, sting of tearing eyes, loss of taste, and the inability to close your eyes.*

*CLAIMS BASED ON TRADITIONAL HOMEOPATHIC PRACTICE, NOT ACCEPTED MEDICAL EVIDENCE. NOT FDA EVALUATED.

This product is not intended to diagnose, treat, cure, or prevent any disease.

Uses

Temporarily supports your body when dealing with loss of movement in the face, facial drooping and distortion, sting of tearing eyes, loss of taste, and the inability to close your eyes.*

*CLAIMS BASED ON TRADITIONAL HOMEOPATHIC PRACTICE, NOT ACCEPTED MEDICAL EVIDENCE. NOT FDA EVALUATED.

This product is not intended to diagnose, treat, cure, or prevent any disease.

KEEP OUT OF REACH OF CHILDREN

Warnings and Storage:

Ask a professional before use if pregnant or breastfeeding or if you have severe symptoms. Keep away from children. If you have a reaction to this product that is not positive, discontinue use. Store in a cool and dry place.

Warnings and Storage:

Ask a professional before use if pregnant or breastfeeding or if you have severe symptoms. Keep away from children. If you have a reaction to this product that is not positive, discontinue use. Store in a cool and dry place.

*CLAIMS BASED ON TRADITIONAL HOMEOPATHIC PRACTICE, NOT ACCEPTED MEDICAL EVIDENCE. NOT FDA EVALUATED.

This product is not intended to diagnose, treat, cure, or prevent any disease.

Entire package label